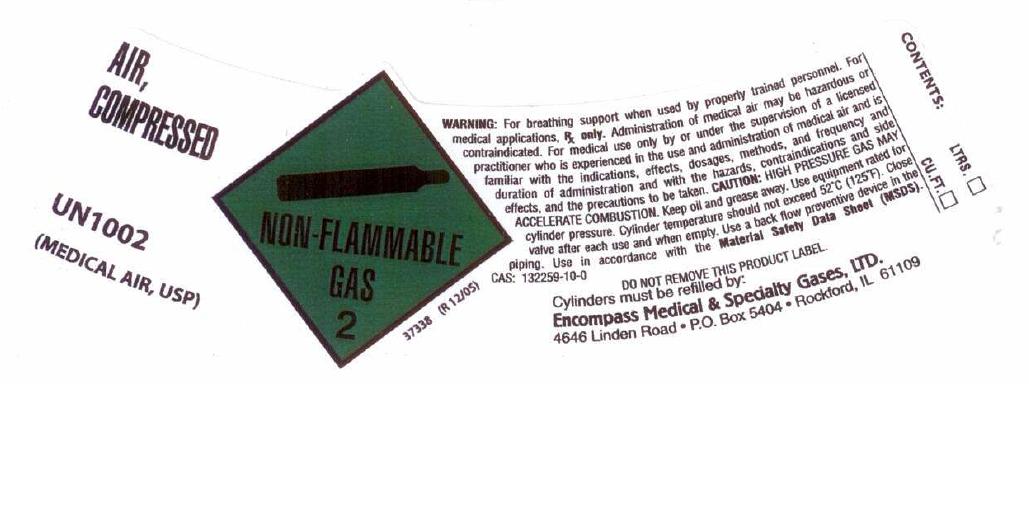 DRUG LABEL: Air
NDC: 48883-005 | Form: GAS
Manufacturer: Encompass Medical & Specialty Gases, Ltd.
Category: prescription | Type: HUMAN PRESCRIPTION DRUG LABEL
Date: 20101208

ACTIVE INGREDIENTS: Air 1000 mL/1 L

Air Label

PACKAGE LABEL

AIR, COMPRESSED UN1002
MEDICAL AIR USP
Distributed by Linde Gas 2883 Simpson Circle Norcross, GA 30071
NON-FLAMMABLE GAS 2
MEDICAL GAS LifeGas
WARNING: For breathing support when used by properly trained personnel. For medical applications, Rx only.
Administration of medical air may be hazardous or contraindicated. For use only by or under supervision of a licensed practitioner who is experienced in the use and administration of medical air and is familiar with the indications, effects, dosages, methods, and frequency and duration of administration, and with the hazards, contraindications, and side effects and the precautions to be taken. CAUTION: HIGH PRESSURE COMPRESSED GAS MAY ACCELERATE COMBUSTION. Open valve slowly and close after each use. Keep away from heat. Keep oil, grease and other combustibles away. Do not strike arc or laser beam on cylinder. Use equipment rated for cylinder pressure. Use a back flow preventive device in the piping. Cylinder temperatures should not exceed 52C (125F). Always secure cylinder in upright position. Return cylinder with 25 PSIG pressure. Return cylinder with cylinder cap secured, if applicable. Use this product in accordance with its specific Material Safety Data Sheet, available at Web Site: www.us.lindegas.com.
CAS: 132259-10-0
DO NOT REMOVE THIS PRODUCT LABEL. LG050B
CONTENTS: Cylinder Type K M E D
Liters 6056 3000 679 396